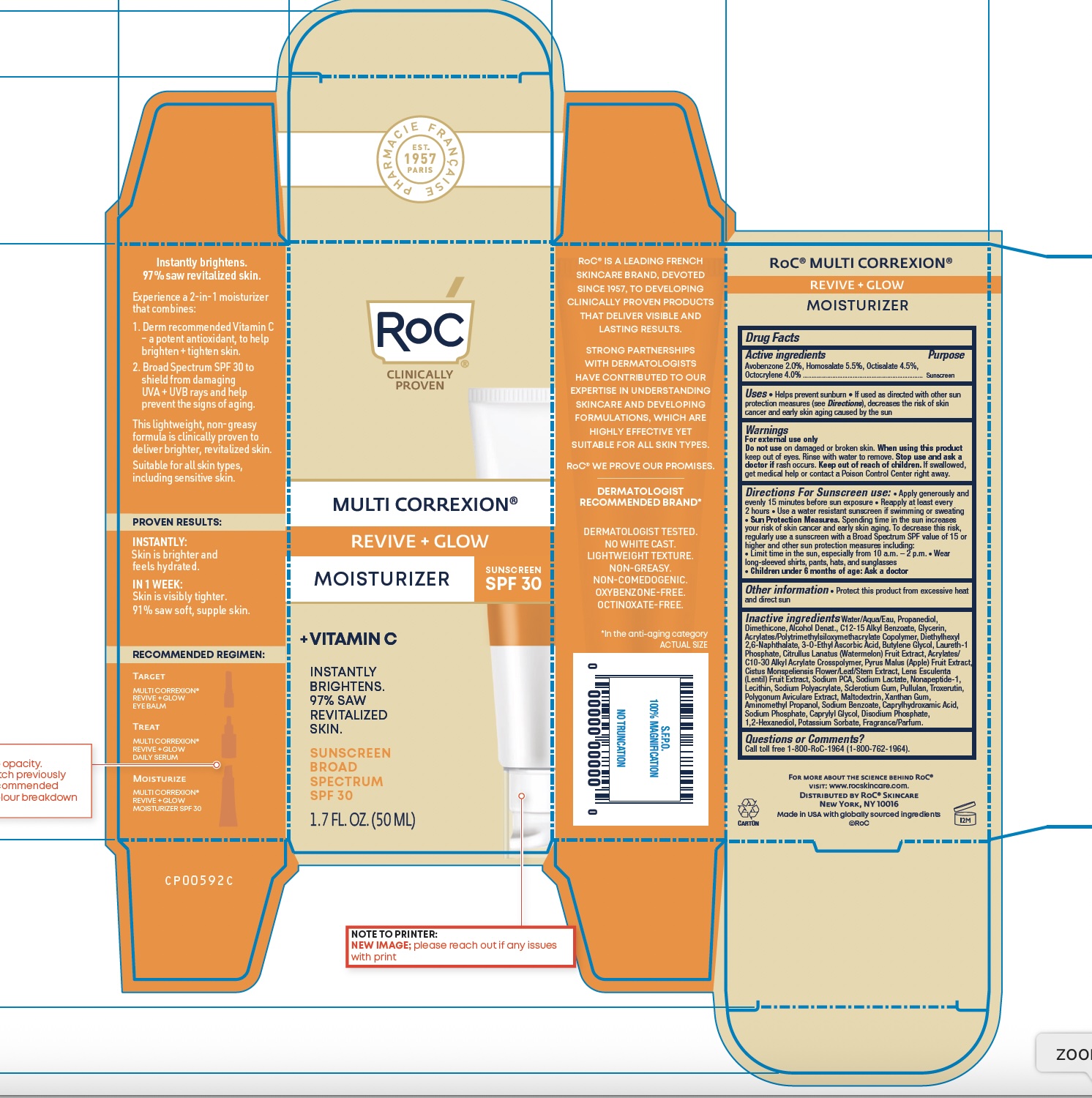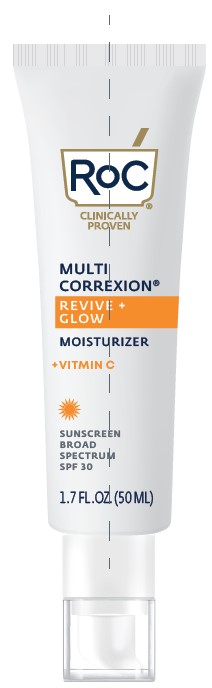 DRUG LABEL: RoC Multi Correxion Revive and Glow Moisturizer SPF 30
NDC: 73496-013 | Form: LOTION
Manufacturer: RoC Skincare
Category: otc | Type: HUMAN OTC DRUG LABEL
Date: 20251209

ACTIVE INGREDIENTS: AVOBENZONE 2 g/100 mL; OCTISALATE 4.5 g/100 mL; OCTOCRYLENE 4 g/100 mL; HOMOSALATE 5.5 g/100 mL
INACTIVE INGREDIENTS: POLYGONUM AVICULARE TOP; XANTHAN GUM; AMINOMETHYLPROPANOL; WATER; WATERMELON; PULLULAN; PROPANEDIOL; DIMETHICONE; SODIUM PYRROLIDONE CARBOXYLATE; ALCOHOL; DIETHYLHEXYL 2,6-NAPHTHALATE; 3-O-ETHYL ASCORBIC ACID; APPLE; CISTUS INCANUS FLOWERING TOP; SODIUM LACTATE; NONAPEPTIDE-1; LECITHIN, SOYBEAN; BETASIZOFIRAN; CAPRYLYL GLYCOL; SODIUM PHOSPHATE, DIBASIC, ANHYDROUS; 1,2-HEXANEDIOL; SODIUM POLYACRYLATE (2500000 MW); MALTODEXTRIN; SODIUM PHOSPHATE; CAPRYLHYDROXAMIC ACID; LAURETH-1 PHOSPHATE; BUTYLENE GLYCOL; ALKYL (C12-15) BENZOATE; GLYCERIN; LENS CULINARIS FRUIT; TROXERUTIN; BUTYL ACRYLATE/METHYL METHACRYLATE/TRIMETHYLSILOXYMETHACRYLATE COPOLYMER; ACRYLATES/C10-30 ALKYL ACRYLATE CROSSPOLYMER (60000 MPA.S AT 0.5%)

RoC Multi Correxion Revive + Glow Moisturizer SPF 30

OTC Actives

Active Ingredients Purpose

Avobenzone 2.0%, Homosalate 5.5%, Octisalate 4.5%, Octocrylene 4.0% Sunscreen

Uses

Uses • Helps prevent sunburn • If used as directed with other sun protection measures (see Directions), decreases the risk of skin cancer and early skin aging caused by the sun.

Warnings

Warnings For external use only. Do not use on damaged or broken skin. When using this product keep out of eyes. Rinse with water to remove. Stop use and ask a doctor if rash occurs. Keep out of reach of children. If swallowed, get medical help or contact a Poison Control Center right away.

Keep out of reach of children. If swallowed, get medical help or contact a Poison Control Center right away.

Indications and Usage

Helps prevent sunburn • If used as directed with other sun protection measures (see Directions), decreases the risk of skin cancer and early skin aging caused by the sun.

Directions For Sunscreen use: • Apply generously and evenly 15 minutes before sun exposure • Reapply at least every 2 hours • Use a water resistant sunscreen if swimming or sweating • Sun Protection Measures. Spending time in the sun increases your risk of skin cancer and early skin aging. To decrease this risk, regularly use a sunscreen with a Broad Spectrum SPF value of 15 or higher and other sun protection measures including: • Limit time in the sun, especially from 10 a.m. – 2 p.m. • Wear long-sleeved shirts, pants, hats, and sunglasses • Children under 6 months of age: Ask a doctor.

Other information

Other information Protect this product from excessive heat and direct sun • May stain some fabrics.

Inactive Ingredients

Water, Propanediol, Dimethicone, Alcohol Denat., C12-15 Alkyl Benzoate, Glycerin, Acrylates/Polytrimethylsiloxymethacrylate Copolymer, Diethylhexyl 2,6-Naphthalate, 3-O-Ethyl Ascorbic Acid, Butylene Glycol, Citrullus Lanatus (Watermelon) Fruit Extract, Acrylates/C10-30 Alkyl Acrylate Crosspolymer, Pyrus Malus (Apple) Fruit Extract, Cistus Monspeliensis Flower/Leaf/Stem Extract, Lens Esculenta (Lentil) Fruit Extract, Sodium PCA, Sodium Lactate, Nonapeptide-1, Lecithin, Polygonum Aviculare Extract, Troxerutin, Laureth-1 Phosphate, Sodium Polyacrylate, Sclerotium Gum, Pullulan, Maltodextrin, Xanthan Gum, Aminomethyl Propanol, Sodium Phosphate, Caprylyl Glycol, Disodium Phosphate, 1,2-Hexanediol, Caprylhydroxamic Acid, Fragrance.

Questions or comments?

Call toll free 1-800-RoC-1964 (1-800-762-1964).